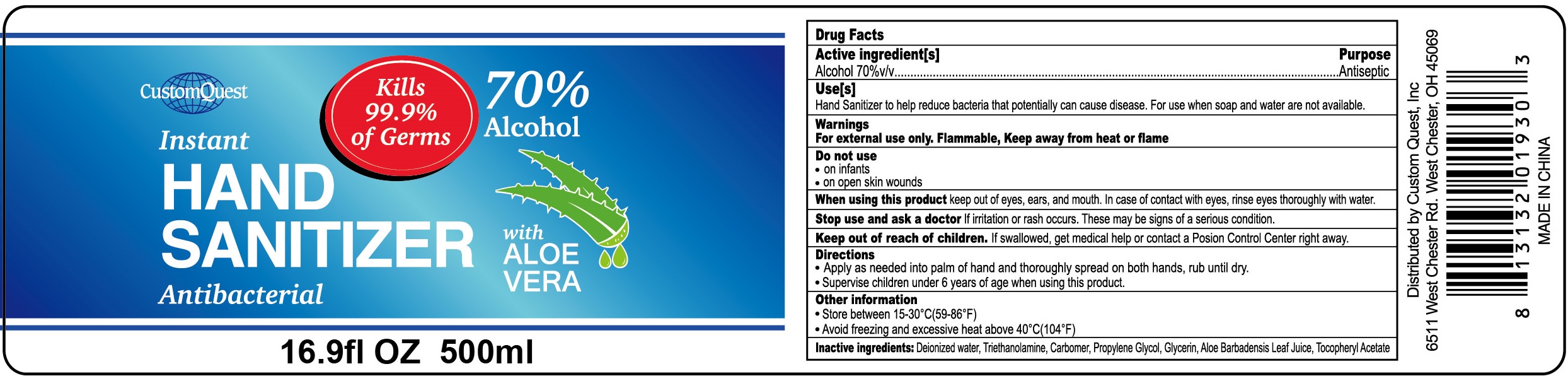 DRUG LABEL: CustomQuest Instant Hand Sanitizer with Aloe Vera
NDC: 52174-107 | Form: GEL
Manufacturer: Ningbo BST Clean And Care Products Co., Ltd
Category: otc | Type: HUMAN OTC DRUG LABEL
Date: 20200428

ACTIVE INGREDIENTS: alcohol 70 mL/100 mL
INACTIVE INGREDIENTS: WATER; PROPYLENE GLYCOL; ALOE VERA LEAF; CARBOMER 934; GLYCERIN; TROLAMINE

Drug facts

Active ingredient(s) Purpose

Alcohol 70% v/v ............... Antiseptic

PURPOSE

Hand sanitizer to help reduce bacteria that potentially can cause disease. For use when soap and water are not available.

KEEP OUT OF REACH OF CHILDREN

if swallowed, get medical help or contact a Posion Control Center right away.

INDICATIONS AND USAGE

- Apply as needed into palm of hand and thoroughly spread on both hands, rub until dry.
- Supervise children under 6 years of age when using this product.

WARNINGS

For external use only.
Flammable. Keep away from heat or flame.

When using this product keep out of eyes, ears, and mouth. In case of contact with eyes, rinse eyes thoroughly with water.

Stop using and ask a doctor if irritation or rash occurs. These may be signs of a serious condition.

Do not use

- On infants
- On open skin wounds

DOSAGE AND ADMINISTRATION

Pump as needed into your palms and thoroughly spread on both hands, and rub the skin until dry.

Other information:

- Store between 15-30℃（59-86℉）
- Avoid freezing and excessive heat above 40℃（104℉）

INACTIVE INGREDIENT

Deionizer Water, Triethanolamine, Carbomer, Propylene Glycol, Glycerin, Aloe Barbadensis Leaf Juice, Tocopheryl Acetate